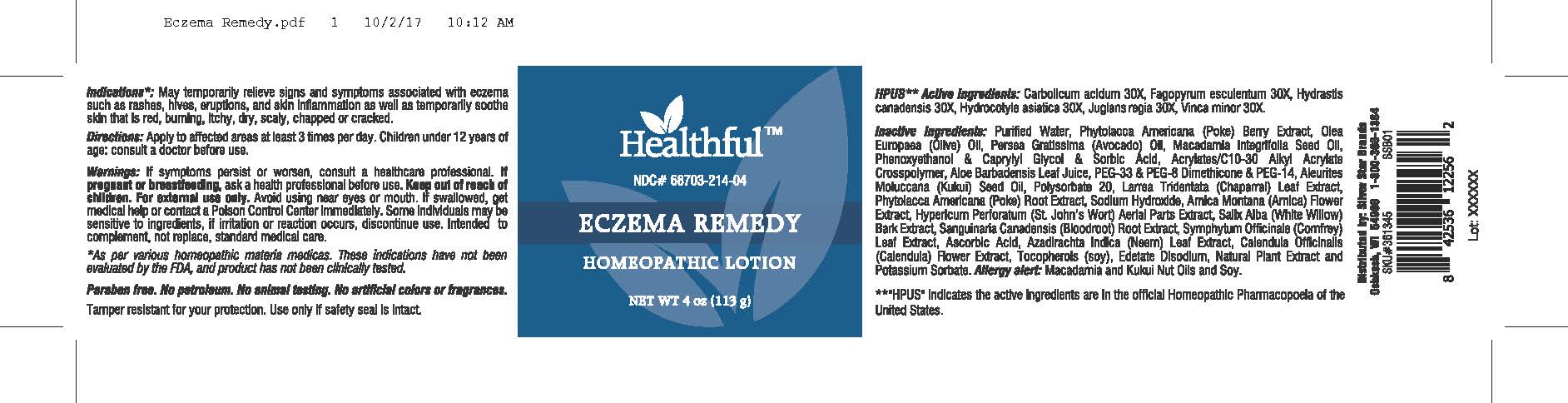 DRUG LABEL: Eczema Remedy
NDC: 68703-214 | Form: LOTION
Manufacturer: Silver Star Brands
Category: homeopathic | Type: HUMAN OTC DRUG LABEL
Date: 20230304

ACTIVE INGREDIENTS: PHENOL 30 [hp_X]/113 g; CENTELLA ASIATICA 30 [hp_X]/113 g; FAGOPYRUM ESCULENTUM 30 [hp_X]/113 g; JUGLANS REGIA LEAF 30 [hp_X]/113 g; VINCA MINOR 30 [hp_X]/113 g; HYDRASTIS CANADENSIS WHOLE 30 [hp_X]/113 g
INACTIVE INGREDIENTS: ASCORBIC ACID; AZADIRACHTA INDICA LEAF; SANGUINARIA CANADENSIS ROOT; PHENOXYETHANOL; CAPRYLYL GLYCOL; SORBIC ACID; ARNICA MONTANA FLOWER; MACADAMIA ACID; ALOE VERA LEAF; POLYETHYLENE GLYCOL 1500; KUKUI NUT OIL; LARREA TRIDENTATA LEAF; HYPERICUM PERFORATUM; CARBOMER INTERPOLYMER TYPE A (ALLYL SUCROSE CROSSLINKED); POLYSORBATE 20; PHYTOLACCA AMERICANA ROOT; SALIX ALBA BARK; PEG-8 DIMETHICONE; POLYETHYLENE GLYCOL 700; SODIUM HYDROXIDE; POTASSIUM SORBATE; EDETATE DISODIUM; COMFREY LEAF; CALENDULA OFFICINALIS FLOWER; TOCOPHEROL; AVOCADO OIL; WATER; PHYTOLACCA AMERICANA FRUIT; BLACK OLIVE

Healthful™ Eczema Remedy

HPUS** Active Ingredients: Carbolicum acidum 30X, Fagopyrum esculentum 30X, Hydrastis canadensis 30X, Hydrocotyle asiatica 30X, Juglans regia 30X, Vinca minor 30X.

**"HPUS" indicates the active ingredients are in the official Homeopathic Pharmacopoeia of the United States.

Uses*

Indications*: May temporarily relieve signs and symptoms associated with eczema such as rashes, hives, eruptions, and skin inflammation as well as temporarily soothe skin that is red, burning, itchy, dry, scaly, chapped or cracked.

*As per various homeopathic materia medicas. These indications have not been evaluated by the FDA, and product has not been clinically tested.

Warnings

Warnings: If symptoms persist or worsen, consult a healthcare professional. If pregnant or breastfeeding, ask a health professional before use. Keep out of reach of children. For external use only. Avoid using near eyes or mouth. If swallowed, get medical help or contact a Poison Control Center immediately. Some individuals may be sensitive to ingredients, if irritiation or reaction occurs, discontinue use. Intended to complement, not replace, standard medical care.

Directions

Apply to affected areas at least 3 times per day. Children under 12 years of age: consult a doctor before use.

OTHER SAFETY INFORMATION

Paraben free. No petroleum. No animal testing. No artificial colors or fragrances.

Tamper resistant for your protection. Use only if safety seal is intact.

Inactive Ingredients

Purified Water, Phytolacca Americana (Poke) Berry Extract, Olea Europaea (Olive) Oil, Persea Gratissima (Avocado) Oil, Macadamia Integrifolia Seed Oil, Phenoxyethanol & Caprylyl Glycol & Sorbic Acid, Acrylates/C10-30 Alkyl Acrylate Crosspolymer, Aloe Barbadensis Leaf Juice, PEG-33 & PEG-8 Dimethicone & PEG-14, Aleurites Moluccana (Kukui) Seed Oil, Polysorbate 20, Larrea Tridentata (Chaparral) Leaf Extract, Phytolacca Americana (Poke) Root Extract, Sodium Hydroxide, Arnica Montana (Arnica) Flower Extract, Hypericum Perforatum (St. John's Wort) Aerial Parts Extract, Salix Alba (White Willow) Bark Extract, Ascorbic Acid, Azadirachta Indica (Neem) Leaf Extract, Calendula Officinalis (Calendula) Flower Extract, Tocopherols (soy), Edetate Disodium, Natural Plant Extract and Potassium Sorbate. Allergy alert: Macadamia and Kukui Nut Oils and Soy.

Keep out of reach of children.

PREGNANCY OR BREAST FEEDING

If pregnant or breastfeeding, ask a health professional before use.

PURPOSE

Homeopathic Lotion